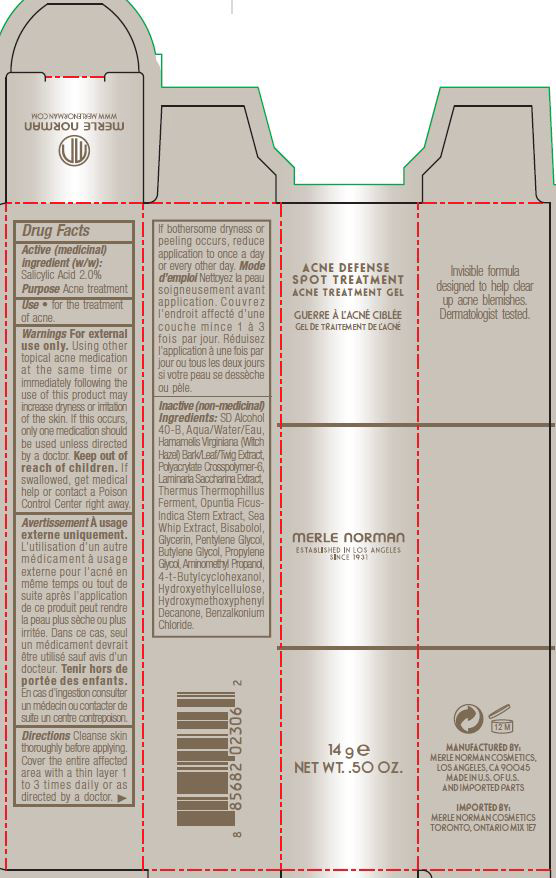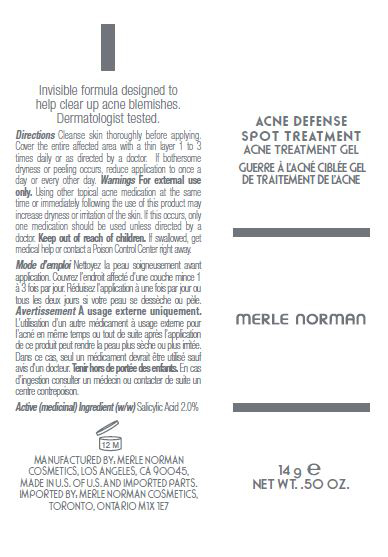 DRUG LABEL: Acne Defense Spot Treatment
NDC: 57627-201 | Form: GEL
Manufacturer: Merle Norman Cosmetics, Inc
Category: otc | Type: HUMAN OTC DRUG LABEL
Date: 20251118

ACTIVE INGREDIENTS: SALICYLIC ACID 2 g/100 g
INACTIVE INGREDIENTS: ALCOHOL; WATER; HAMAMELIS VIRGINIANA TOP; SACCHARINA LATISSIMA; THERMUS THERMOPHILUS LYSATE; OPUNTIA FICUS-INDICA STEM; PSEUDOPTEROGORGIA ELISABETHAE; LEVOMENOL; GLYCERIN; PENTYLENE GLYCOL; BUTYLENE GLYCOL; PROPYLENE GLYCOL; AMINOMETHYLPROPANOL; 4-TERT-BUTYLCYCLOHEXANOL; HYDROXYETHYL CELLULOSE (100 MPA.S AT 2%); 1-(4-HYDROXY-3-METHOXYPHENYL)-DECAN-3-ONE; BENZALKONIUM CHLORIDE

Acne Defense Spot Treatment

Active Ingredient: Purpose

Salicylic Acid 2.0% Acne Treatment

PURPOSE

For the treatment of Acne

Keep out of reach of children.If swallowed, get medical help or contact a Poison Control Center right away

INDICATIONS AND USAGE

Using other topical acne medication at the same tim or immediately following the use of this product may increase dryness or irritation of the skin. If this occurs, only one medication should be used unless directed by a doctor

WARNINGS

- For external use only

DOSAGE AND ADMINISTRATION

Cleanse skin thoroughly before applying. Cover the entire affected area with a thing layer 1 to 3 times daily or as directed by a doctor. If bothersome dryness or peeling occurs, reduce application to once a day or every other day.

INACTIVE INGREDIENT

SD Alcohol 40-B, Aqua/Water/Eau, Hamamelis Virginiana (Witch Hazel) Bark/Leaf/Twig Extract, Polyacrylate Crosspolymer 6, Laminaria Saccarina Extract, Thermus Thermophillus Ferment, Opuntia Ficus-Indica Stem Extract, Sea Whip Extract, Bisabolol, Glycerin, Pentylene Glycol, Butylene Glycol, Propylene Glycol, Aminomethyl Propanol, 4-t-Butylcyclohexanol, Hydroxyethylcellulose, Hydroxymethoxyphenyl Decanone, Benzalkonium Chloride

PACKAGE LABEL

ACNE DEFENSE

SPOT TREATMENT

ACNE TREATMENT GEL

merle norman

14g e

NET WT. .50 OZ.